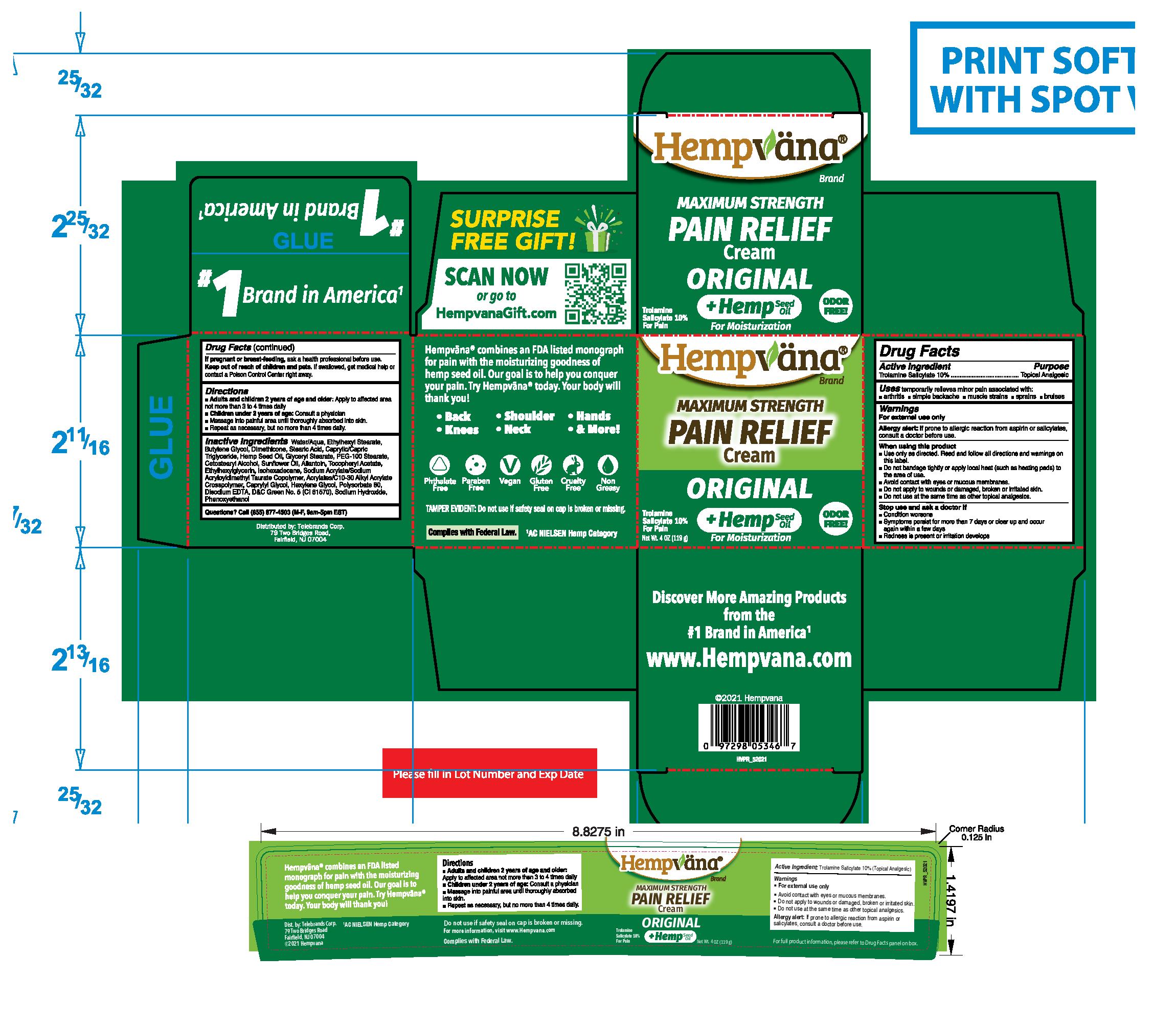 DRUG LABEL: Hempvana

NDC: 73287-001 | Form: CREAM
Manufacturer: Telebrands Corp
Category: otc | Type: HUMAN OTC DRUG LABEL
Date: 20241120

ACTIVE INGREDIENTS: TROLAMINE SALICYLATE 10 g/100 g
INACTIVE INGREDIENTS: WATER; ETHYLHEXYL STEARATE; BUTYLENE GLYCOL; DIMETHICONE; STEARIC ACID; MEDIUM-CHAIN TRIGLYCERIDES; CANNABIS SATIVA SEED OIL; GLYCERYL MONOSTEARATE; PEG-100 STEARATE; CETOSTEARYL ALCOHOL; SUNFLOWER OIL; ALLANTOIN; .ALPHA.-TOCOPHEROL ACETATE, DL-; ETHYLHEXYLGLYCERIN; ISOHEXADECANE; SODIUM ACRYLATE/SODIUM ACRYLOYLDIMETHYLTAURATE COPOLYMER (4000000 MW); CARBOMER COPOLYMER TYPE A (ALLYL PENTAERYTHRITOL CROSSLINKED); CAPRYLYL GLYCOL; HEXYLENE GLYCOL; POLYSORBATE 80; EDETATE DISODIUM ANHYDROUS; D&C GREEN NO. 5; SODIUM HYDROXIDE; PHENOXYETHANOL

Hempvana Pain Relief Cream

Active Ingredient:

Trolamine Salicylate 10%

Purpose

Trolamine Salicylate 10%................Topical Analgesic

Uses

temporarily relieves minor pain associated with:

• arthritis • simple backache • muscle strains • sprains • bruises

Warnings

For external use only

Allergy alert:If prone to allergic reaction from aspirin or salicylates, consult a doctor before use.

When using this product

- Use only as directed. Read and follow all directions and warnings on this label.
- Do not bandage tightly or apply local heat (such as heating pads) to the area of use.
- Avoid contact with eyes or mucous membranes.
- Do not apply to wounds or damaged, broken or irritated skin.
- Do not use at the same time as other topical analgesics.

Stop use and ask a doctor if

- Condition worsens
- Symptoms persist for more than 7 days or clear up and occur again within a few days
- Redness is present or irritation develops

PREGNANCY OR BREAST FEEDING

If pregnant or breast-feeding, ask a health professional before use.

Keep out of reach of children and pets.If swallowed, get medical help or contact a Poison Control Center right away.

Directions

- Adults and children 2 years of age and older:Apply to affected area not more than 3 to 4 times daily
- Children under 2 years of age:Consult a physician
- Massage into painful area until thoroughly absorbed into skin.
- Repeat as necessary, but no more than 4 times daily.

Inactive Ingredients

Water/Aqua, Ethylhexyl Stearate, Butylene Glycol, Dimethicone, Stearic Acid, Caprylic/Capric Triglyceride, Hemp Seed Oil (Hemp Seed Oil), Glyceryl Stearate, PEG-100 Stearate, Cetostearyl Alcohol, Sunflower Oil, Allantoin, Tocopheryl Acetate, Ethylhexylglycerin, Isohexadecane, Sodium Acrylate/Sodium Acryloyldimethyl Taurate Copolymer, Acrylates/C10-30 Alkyl Acrylate Crosspolymer, Caprylyl Glycol, Hexylene Glycol, Polysorbate 80, Disodium EDTA, D&C Green No. 5 (CI 61570), Sodium Hydroxide, Phenoxyethanol

Questions?

Call (855) 877-4503 (M-F, 9am-5pm EST)

DESCRIPTION

Hempvana®Pain Relief Cream absorbs quickly and goes to work instantly. Its unique formula includes a proven active ingredient plus the moisturizing benefit of cold pressed hemp seed* extract for soothing relief to back, neck, shoulders, feet, wrists, calves and more.

- Maximum Strength
- Odor Free
- Non-Irritating
- No Burning
- Non Greasy

TAMPER EVIDENT: Do not use if safety seal on cap is broken or missing.

For more information, visit www.HempvanaStore.com

*Complies with Federal Law. Hemp seed extract in the form of oil made by cold-pressing industrial hemp seeds.

cultivar.

Dist. by: Telebrands Corp.

79 Two Bridges Road,

Fairfield, NJ 07004

Packaging

Hempvana

Maximum Strength

Pain Relief

Cream

Original

+Hemp Seed Oil

Trolamine Salicylate 10% For Pain

Odor Free!

Net Wt. 4 OZ (119 g)